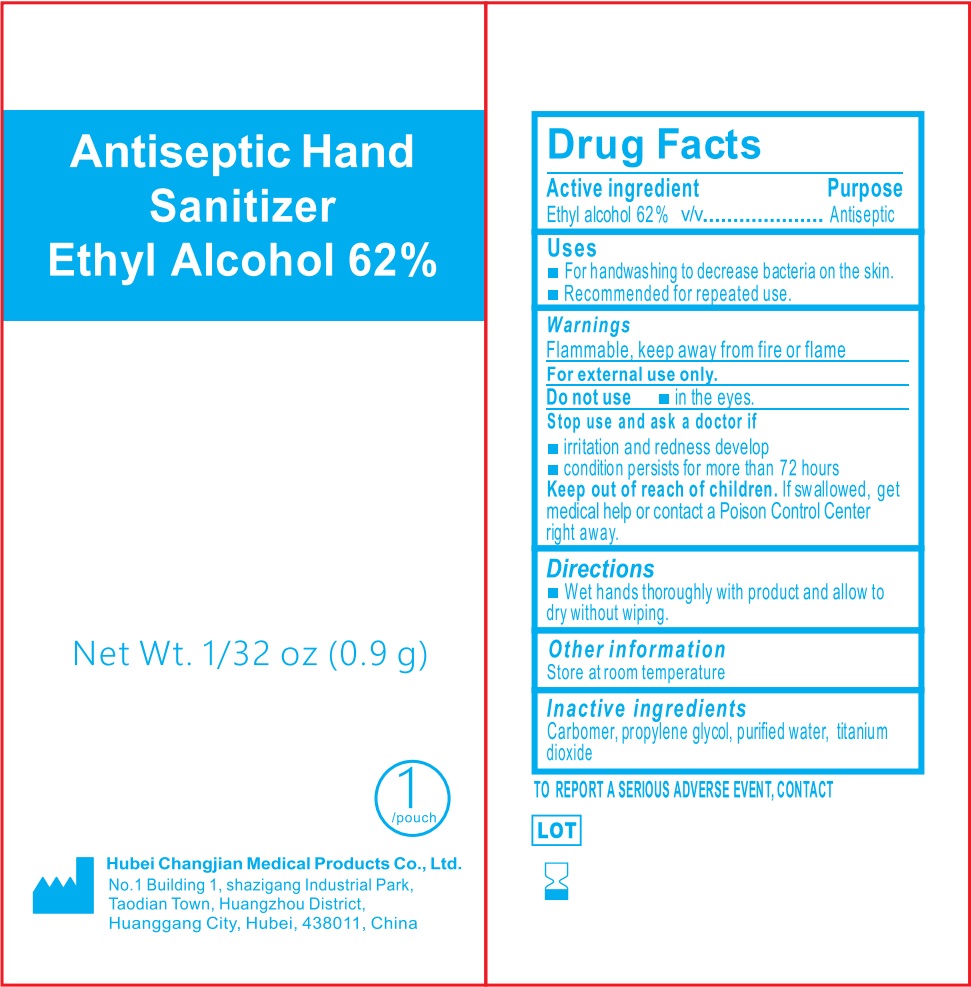 DRUG LABEL: Antiseptic Hand Sanitizer
NDC: 82996-005 | Form: LIQUID
Manufacturer: Hubei Changjian Medical Products Co., Ltd.
Category: otc | Type: HUMAN OTC DRUG LABEL
Date: 20241011

ACTIVE INGREDIENTS: ALCOHOL 620 mg/1 g
INACTIVE INGREDIENTS: WATER

Antiseptic Hand Sanitizer

Active ingredient

Ethyl alcohol 62 % v/v

Purpose

Antiseptic

Uses

- For handwashing to decrease bacteria on the skin.
- Recommended for repeated use.

Warnings

Flammable, keep away from fire or flame
For external use only.

Do not use

in the eyes.

Stop use and ask a doctor if

- irritation and redness develop
- condition persists for more than 72 hours

Keep out of reach of children.

lf swallowed, get medical help or contact a Poison Control Center right away.

Directions

- Wet hands thoroughly with product and allow to dry without wiping.

Other information

Store at room temperature

Inactive ingredients

Carbomer, propylene glycol, purified water, titanium dioxide